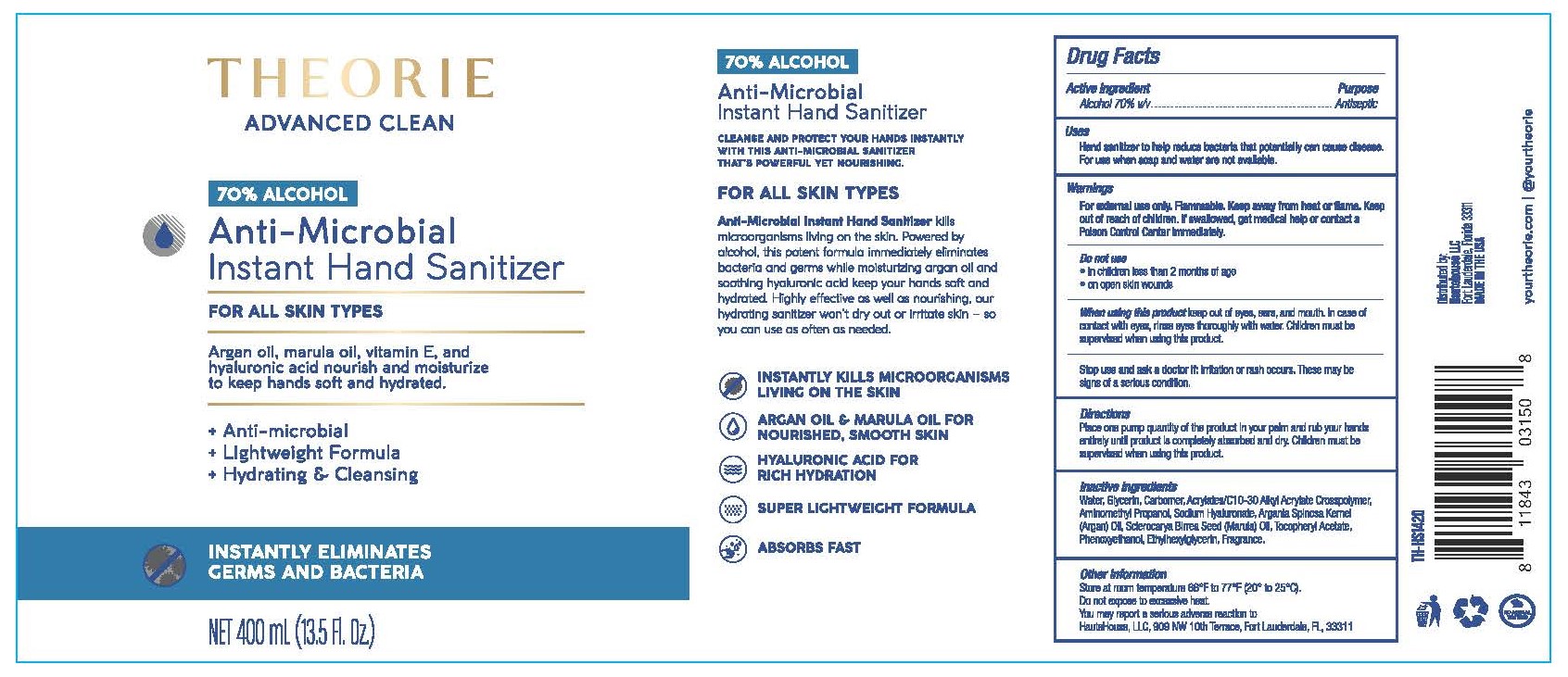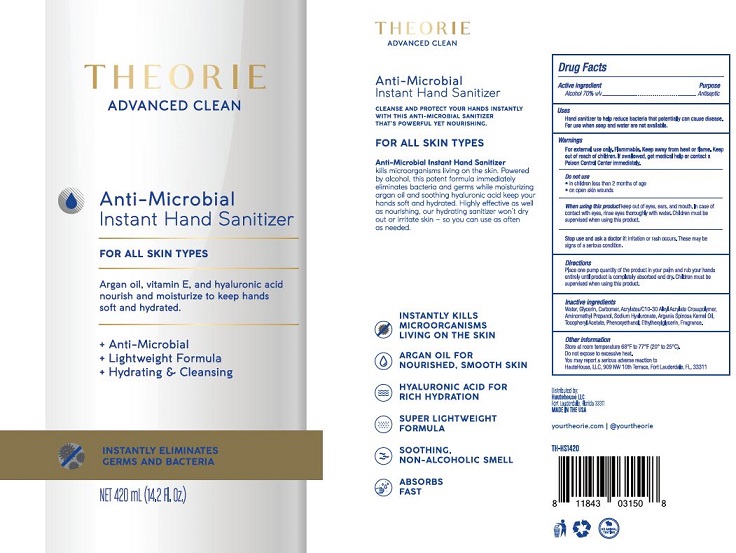 DRUG LABEL: THEORIE Anti-Microbial Instant Hand Sanitizer
NDC: 73857-001 | Form: GEL
Manufacturer: Dynastis, LLC
Category: otc | Type: HUMAN OTC DRUG LABEL
Date: 20200814

ACTIVE INGREDIENTS: ALCOHOL .7 L/1 L
INACTIVE INGREDIENTS: WATER; GLYCERIN; CARBOMER 940; CARBOMER INTERPOLYMER TYPE A (ALLYL SUCROSE CROSSLINKED); AMINOMETHYLPROPANOL; HYALURONATE SODIUM; ARGAN OIL; .ALPHA.-TOCOPHEROL ACETATE, DL-; PHENOXYETHANOL; ETHYLHEXYLGLYCERIN

THEORIE Anti-Microbial Instant Hand Sanitizer

DRUG FACTS

Alcohol 70% v/v - Antiseptic

Uses:

Hand sanitizer to help reduce bacteria that potentially can cause disease. For use when soap and water are not available.

Warnings:

For external use only. Flammable. Keep away from heat or flame.

If swallowed, get medical help or contact a Poison Control Center immediately.

KEEP OUT OF REACH OF CHILDREN SECTION

Do not use:

• in children less than 2 months of age
• on open skin wounds

When using this product keep out of eyes, ears, and mouth. In case of contact with eyes, rinse eyes thoroughly with water. Children must be supervised when using this product.

Stop use and ask a doctor if: irritation or rash occurs. These maybe signs of a serious condition.

Directions:

Place one pump quantity of the product in you palm and rub your hands entirely until product is completely absorbed and dry. Children must be supervised when using this product.

Inactive Ingredients:

Water, Glycerin, Carbomer, Acrylates/C10-30 Alkyl Acrylate Crosspolymer, Aminomethyl Propanol, Sodium Hyaluronate, Argania Spinosa Kernel (Argan) Oil, Tocopheryl Acetate, Phenoxyethanol, Ethylhexylglycerin, Fragrance.

Other Information:

Store at room temperature 68°F to 77°F (20° to 25°C)
Do not expose to excessive heat.
You may report a serious adverse reaction to: Hautehouse, LLC, 909 NW Terrace, Fort Lauderdale, FL 33311 USA

For Questions:

HAUTEHOUSE INC.
909 NW Terrace
Fort Lauderdale, FL 33311 USA
+1 (954) 376-8966
www.hautehouse.com